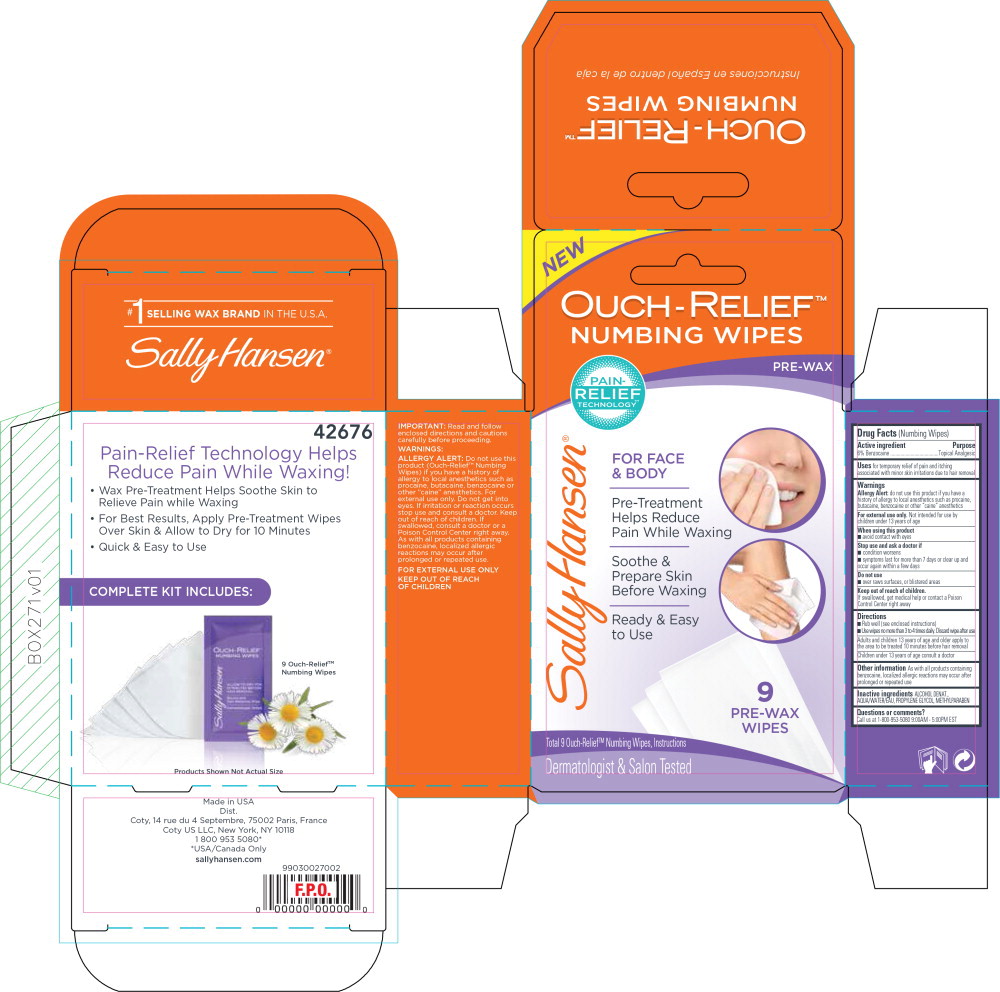 DRUG LABEL: Sally Hansen Ouch-Relief Numbing Wipes
NDC: 66184-156 | Form: CLOTH
Manufacturer: Coty US LLC
Category: otc | Type: HUMAN OTC DRUG LABEL
Date: 20211019

ACTIVE INGREDIENTS: BENZOCAINE 0.0543 g/1 1
INACTIVE INGREDIENTS: ALCOHOL; WATER; DENATONIUM BENZOATE; PROPYLENE GLYCOL; METHYLPARABEN

Drug Facts (Numbing Wipes)

Active ingredient

6% Benzocaine

Purpose

Topical Analgesic

Uses

for temporary relief of pain and itching associated with minor skin irritations due to hair removal

Warnings

Allergy Alert: do not use this product if you have a history of allergy to local anesthetics such as procaine, butacaine, benzocaine or other "caine" anesthetics

For external use only. Not intended for use by children under 13 years of age

When using this product

- avoid contact with eyes

Stop use and ask a doctor if

- condition worsens
- symptoms last for more than 7 days or clear up and occur again within a few days

Do not use

- over raws surfaces, or blistered areas

Keep out of reach of children.

If swallowed, get medical help or contact a Poison Control Center right away

Directions

- Rub well (see enclosed instructions)
- Use wipes no more than 3 to 4 times daily. Discard wipe after use

Adults and children 13 years of age and older apply to :he area to be treated 10 minutes before hair removal Children under 13 years of age consult a doctor

Other information

As with all products containing benzocaine, localized allergic reactions may occur after prolonged or repeated use

Inactive ingredients

ALCOHOL DENAT., AQUA/WATER/EAU, PROPYLENE GLYCOL, METHYLPARABEN

Questions or comments?

Call us at 1-800-953-5080 9:00AM - 5:00PM EST

Principal Display Panel - Carton Label

OUCH-RELIEF™
NUMBING WIPES

PRE-WAX

PAIN-
RELIEF
TECHNOLOGY

FOR FACE
& BODY

Pre-Treatment
Help Reduce
Pain While Waxing

Soothe &
Prepare Skin
Before Waxing

Ready & Easy
to Use

9
PRE-WAX
WIPES

Total 9 Ouch-Relief™ Numbing Wipes, Instructions

Dermatologist & Salon Tested